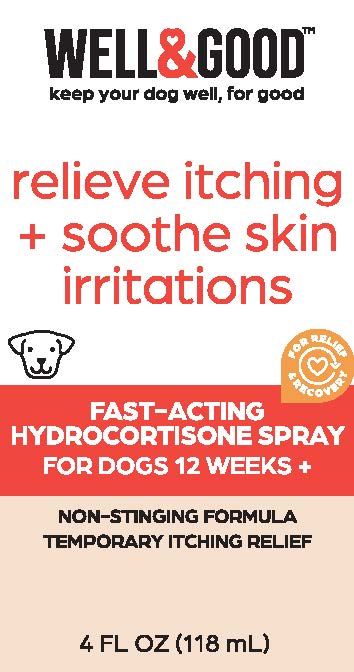 DRUG LABEL: Well and Good Relieve Itching and Soothe Skin Irritations
NDC: 77720-030 | Form: SPRAY
Manufacturer: Skaffles Group Limited Liability Company
Category: animal | Type: OTC ANIMAL DRUG LABEL
Date: 20221215

ACTIVE INGREDIENTS: HYDROCORTISONE ACETATE 0.5 g/100 mL
INACTIVE INGREDIENTS: WATER; DIMETHYL SULFOXIDE; PROPYLENE GLYCOL

Hydrocortisone Spray

Drug Facts

Active Ingredient

Hydrocortisone Acetate 0.50%

Purpose

Anti-itch

Uses

To soothe: ■ itching ■ flea and insect bites ■ skin irritations

The WELL & GOOD FAST-ACTING
HYDROCORTISONE SPRAY offers
your dog sweet relief in no time
with a non-stinging formula that's
ideal for bug bites, dermatitis,
eczema, and other skin irritations.

IDEAL FOR BUG BITES

SOOTHES DERMATITIS, ECZEMA AND OTHER SKIN IRRITATIONS

Warnings

For external use only on adult dogs. Keep out of
reach of children and animals to avoid unintended
consumption.

Do not use in eyes or nose. Not for
prolonged use. Do not apply to large areas of the
body. Do not use where infection (pus) is present,
since the drug may allow infection to be spread. Do
not use on pregnant animals. Do not use if product
appears to be tampered with.

Stop use and ask
veterinarian if redness, irritation, or swelling
persists or increases.

Directions

■ shake well before use
■ hold sprayer 4-6 inches from the affected area
and spray directly
■ apply 2-3 times until relief is achieved
■ for best results, cleanse affected area prior to
using this product
■ avoid contact with the eyes

Other Information: Store product in cool, dry
place. Avoid temperatures above 86° F.

Inactive Ingredients

Deionized Water, Propylene Glycol USP, Dimethyl Sulfoxide.

Principal Display Panel

WELL&GOOD™
keep your pet well, for good

relieve itching + soothe skin irritations

For Relief & Recovery

FAST ACTING HYDROCORTISONE SPRAY FOR DOGS 12 WEEKS+

NON-STINGING FORMULA
TEMPORARY ITCHING RELIEF

4 FL OZ (118 ml)

CAUTION: FOR TOPICAL PET USE ONLY. NOT INTENDED FOR HUMAN USE. Intended for exlem~ use only. Keep out of reach of children and pets. In case of accidental consumption, contact a healthcare professional immediately. In case of eye contact, rinse thorougly with water. If there is any irritation, discontinue use and seek veterinary care.

Distributed by: International Pet Supplies and Distribution, Inc., San Diego, CA 92127

Contact us at 1.855.FAQ.Petco

©2022 Petco Animal Supplies, Inc.

All Rights Reserved. Made in China